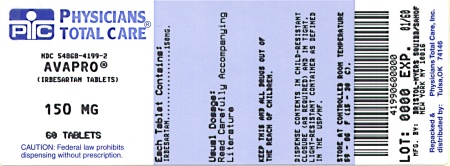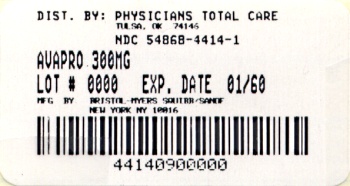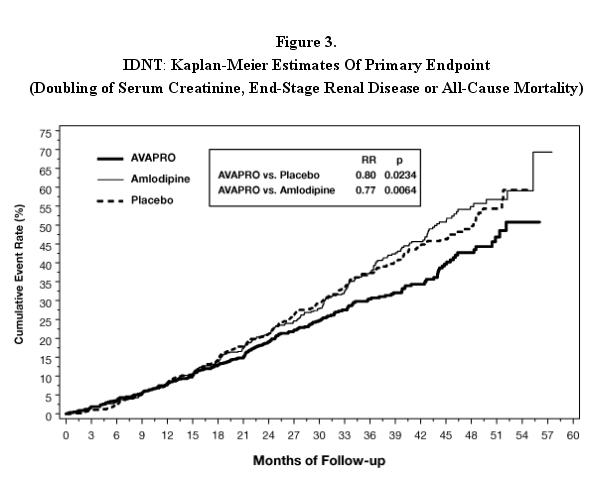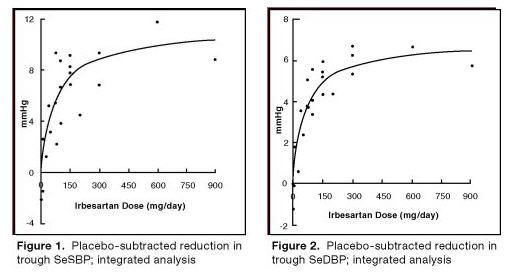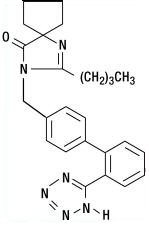 DRUG LABEL: AVAPRO
NDC: 54868-4199 | Form: TABLET
Manufacturer: Physicians Total Care, Inc.
Category: prescription | Type: HUMAN PRESCRIPTION DRUG LABEL
Date: 20111220

ACTIVE INGREDIENTS: irbesartan 150 mg/1 1
INACTIVE INGREDIENTS: lactose; cellulose, microcrystalline; starch, corn; croscarmellose sodium; poloxamer 188; silicon dioxide; magnesium stearate

AVAPRO®
(irbesartan)
Tablets

USE IN PREGNANCY

When used in pregnancy during the second and third trimesters, drugs that act directly on the renin-angiotensin system can cause injury and even death to the developing fetus. When pregnancy is detected, AVAPRO should be discontinued as soon as possible. See WARNINGS: Fetal/Neonatal Morbidity and Mortality.

DESCRIPTION

AVAPRO®* (irbesartan) is an angiotensin II receptor (AT1 subtype) antagonist.

*Registered trademark

Irbesartan is a non-peptide compound, chemically described as a 2-butyl-3-[p-(o-1H-tetrazol-5-ylphenyl)benzyl]-1,3-diazaspiro[4.4]non-1-en-4-one.

Its empirical formula is C25H28N6O, and the structural formula:

Irbesartan is a white to off-white crystalline powder with a molecular weight of 428.5. It is a nonpolar compound with a partition coefficient (octanol/water) of 10.1 at pH of 7.4. Irbesartan is slightly soluble in alcohol and methylene chloride and practically insoluble in water.

AVAPRO is available for oral administration in unscored tablets containing 75 mg, 150 mg, or 300 mg of irbesartan. Inactive ingredients include: lactose, microcrystalline cellulose, pregelatinized starch, croscarmellose sodium, poloxamer 188, silicon dioxide, and magnesium stearate.

CLINICAL PHARMACOLOGY

Mechanism of Action

Angiotensin II is a potent vasoconstrictor formed from angiotensin I in a reaction catalyzed by angiotensin-converting enzyme (ACE, kininase II). Angiotensin II is the principal pressor agent of the renin-angiotensin system (RAS) and also stimulates aldosterone synthesis and secretion by adrenal cortex, cardiac contraction, renal resorption of sodium, activity of the sympathetic nervous system, and smooth muscle cell growth. Irbesartan blocks the vasoconstrictor and aldosterone-secreting effects of angiotensin II by selectively binding to the AT1 angiotensin II receptor. There is also an AT2 receptor in many tissues, but it is not involved in cardiovascular homeostasis.

Irbesartan is a specific competitive antagonist of AT1 receptors with a much greater affinity (more than 8500-fold) for the AT1 receptor than for the AT2 receptor and no agonist activity.

Blockade of the AT1 receptor removes the negative feedback of angiotensin II on renin secretion, but the resulting increased plasma renin activity and circulating angiotensin II do not overcome the effects of irbesartan on blood pressure.

Irbesartan does not inhibit ACE or renin or affect other hormone receptors or ion channels known to be involved in the cardiovascular regulation of blood pressure and sodium homeostasis. Because irbesartan does not inhibit ACE, it does not affect the response to bradykinin; whether this has clinical relevance is not known.

Pharmacokinetics

Irbesartan is an orally active agent that does not require biotransformation into an active form. The oral absorption of irbesartan is rapid and complete with an average absolute bioavailability of 60% to 80%. Following oral administration of AVAPRO, peak plasma concentrations of irbesartan are attained at 1.5 to 2 hours after dosing. Food does not affect the bioavailability of AVAPRO.

Irbesartan exhibits linear pharmacokinetics over the therapeutic dose range.

The terminal elimination half-life of irbesartan averaged 11 to 15 hours. Steady-state concentrations are achieved within 3 days. Limited accumulation of irbesartan (<20%) is observed in plasma upon repeated once-daily dosing.

Metabolism and Elimination

Irbesartan is metabolized via glucuronide conjugation and oxidation. Following oral or intravenous administration of ^14C-labeled irbesartan, more than 80% of the circulating plasma radioactivity is attributable to unchanged irbesartan. The primary circulating metabolite is the inactive irbesartan glucuronide conjugate (approximately 6%). The remaining oxidative metabolites do not add appreciably to irbesartan’s pharmacologic activity.

Irbesartan and its metabolites are excreted by both biliary and renal routes. Following either oral or intravenous administration of ^14C-labeled irbesartan, about 20% of radioactivity is recovered in the urine and the remainder in the feces, as irbesartan or irbesartan glucuronide.

In vitro studies of irbesartan oxidation by cytochrome P450 isoenzymes indicated irbesartan was oxidized primarily by 2C9; metabolism by 3A4 was negligible. Irbesartan was neither metabolized by, nor did it substantially induce or inhibit, isoenzymes commonly associated with drug metabolism (1A1, 1A2, 2A6, 2B6, 2D6, 2E1). There was no induction or inhibition of 3A4.

Distribution

Irbesartan is 90% bound to serum proteins (primarily albumin and α1-acid glycoprotein) with negligible binding to cellular components of blood. The average volume of distribution is 53 liters to 93 liters. Total plasma and renal clearances are in the range of 157 mL/min to 176 mL/min and 3.0 mL/min to 3.5 mL/min, respectively. With repetitive dosing, irbesartan accumulates to no clinically relevant extent.

Studies in animals indicate that radiolabeled irbesartan weakly crosses the blood-brain barrier and placenta. Irbesartan is excreted in the milk of lactating rats.

Special Populations

Gender

No gender-related differences in pharmacokinetics were observed in healthy elderly (age 65-80 years) or in healthy young (age 18-40 years) subjects. In studies of hypertensive patients, there was no gender difference in half-life or accumulation, but somewhat higher plasma concentrations of irbesartan were observed in females (11-44%). No gender-related dosage adjustment is necessary.

Geriatric

In elderly subjects (age 65-80 years), irbesartan elimination half-life was not significantly altered, but AUC and Cmax values were about 20% to 50% greater than those of young subjects (age 18-40 years). No dosage adjustment is necessary in the elderly.

Race

In healthy black subjects, irbesartan AUC values were approximately 25% greater than whites; there were no differences in Cmax values.

Renal Insufficiency

The pharmacokinetics of irbesartan were not altered in patients with renal impairment or in patients on hemodialysis. Irbesartan is not removed by hemodialysis. No dosage adjustment is necessary in patients with mild to severe renal impairment unless a patient with renal impairment is also volume depleted. (See WARNINGS: Hypotension in Volume- or Salt-Depleted Patients and DOSAGE AND ADMINISTRATION.)

Hepatic Insufficiency

The pharmacokinetics of irbesartan following repeated oral administration were not significantly affected in patients with mild to moderate cirrhosis of the liver. No dosage adjustment is necessary in patients with hepatic insufficiency.

Drug Interactions

(See PRECAUTIONS: Drug Interactions.)

Pharmacodynamics

In healthy subjects, single oral irbesartan doses of up to 300 mg produced dose-dependent inhibition of the pressor effect of angiotensin II infusions. Inhibition was complete (100%) 4 hours following oral doses of 150 mg or 300 mg and partial inhibition was sustained for 24 hours (60% and 40% at 300 mg and 150 mg, respectively).

In hypertensive patients, angiotensin II receptor inhibition following chronic administration of irbesartan causes a 1.5- to 2-fold rise in angiotensin II plasma concentration and a 2- to 3-fold increase in plasma renin levels. Aldosterone plasma concentrations generally decline following irbesartan administration, but serum potassium levels are not significantly affected at recommended doses.

In hypertensive patients, chronic oral doses of irbesartan (up to 300 mg) had no effect on glomerular filtration rate, renal plasma flow, or filtration fraction. In multiple dose studies in hypertensive patients, there were no clinically important effects on fasting triglycerides, total cholesterol, HDL-cholesterol, or fasting glucose concentrations. There was no effect on serum uric acid during chronic oral administration, and no uricosuric effect.

Clinical Studies

Hypertension

The antihypertensive effects of AVAPRO (irbesartan) were examined in 7 major placebo-controlled 8 to 12 week trials in patients with baseline diastolic blood pressures of 95 mmHg to 110 mmHg. Doses of 1 mg to 900 mg were included in these trials in order to fully explore the dose-range of irbesartan. These studies allowed comparison of once- or twice-daily regimens at 150 mg/day, comparisons of peak and trough effects, and comparisons of response by gender, age, and race. Two of the 7 placebo-controlled trials identified above examined the antihypertensive effects of irbesartan and hydrochlorothiazide in combination.

The 7 studies of irbesartan monotherapy included a total of 1915 patients randomized to irbesartan (1-900 mg) and 611 patients randomized to placebo. Once-daily doses of 150 mg and 300 mg provided statistically and clinically significant decreases in systolic and diastolic blood pressure with trough (24 hours post-dose) effects after 6 to 12 weeks of treatment compared to placebo, of about 8-10/5-6 mmHg and 8-12/5-8 mmHg, respectively. No further increase in effect was seen at dosages greater than 300 mg. The dose-response relationships for effects on systolic and diastolic pressure are shown in Figures 1 and 2.

Once-daily administration of therapeutic doses of irbesartan gave peak effects at around 3 to 6 hours and, in one ambulatory blood pressure monitoring study, again around 14 hours. This was seen with both once-daily and twice-daily dosing. Trough-to-peak ratios for systolic and diastolic response were generally between 60% to 70%. In a continuous ambulatory blood pressure monitoring study, once-daily dosing with 150 mg gave trough and mean 24-hour responses similar to those observed in patients receiving twice-daily dosing at the same total daily dose.

In controlled trials, the addition of irbesartan to hydrochlorothiazide doses of 6.25 mg, 12.5 mg, or 25 mg produced further dose-related reductions in blood pressure similar to those achieved with the same monotherapy dose of irbesartan. HCTZ also had an approximately additive effect.

Analysis of age, gender, and race subgroups of patients showed that men and women, and patients over and under 65 years of age, had generally similar responses. Irbesartan was effective in reducing blood pressure regardless of race, although the effect was somewhat less in blacks (usually a low-renin population).

The effect of irbesartan is apparent after the first dose, and it is close to its full observed effect at 2 weeks. At the end of an 8-week exposure, about 2/3 of the antihypertensive effect was still present one week after the last dose. Rebound hypertension was not observed. There was essentially no change in average heart rate in irbesartan-treated patients in controlled trials.

Nephropathy in Type 2 Diabetic Patients

The Irbesartan Diabetic Nephropathy Trial (IDNT) was a randomized, placebo- and active-controlled, double-blind, multicenter study conducted worldwide in 1715 patients with type 2 diabetes, hypertension (SeSBP >135 mmHg or SeDBP >85 mmHg), and nephropathy (serum creatinine 1.0 to 3.0 mg/dL in females or 1.2 to 3.0 mg/dL in males and proteinuria ≥900 mg/day). Patients were randomized to receive AVAPRO 75 mg, amlodipine 2.5 mg, or matching placebo once-daily. Patients were titrated to a maintenance dose of AVAPRO 300 mg, or amlodipine 10 mg, as tolerated. Additional antihypertensive agents (excluding ACE inhibitors, angiotensin II receptor antagonists and calcium channel blockers) were added as needed to achieve blood pressure goal (≤135/85 or 10 mmHg reduction in systolic blood pressure if higher than 160 mmHg) for patients in all groups.

The study population was 66.5% male, 72.9% below 65 years of age and 72% White, (Asian/Pacific Islander 5.0%, Black 13.3%, Hispanic 4.8%). The mean baseline seated systolic and diastolic blood pressures were 159 mmHg and 87 mmHg, respectively. The patients entered the trial with a mean serum creatinine of 1.7 mg/dL and mean proteinuria of 4144 mg/day.

The mean blood pressure achieved was 142/77 mmHg for AVAPRO, 142/76 mmHg for amlodipine, and 145/79 mmHg for placebo. Overall, 83.0% of patients received the target dose of irbesartan more than 50% of the time. Patients were followed for a mean duration of 2.6 years.

The primary composite endpoint was the time to occurrence of any one of the following events: doubling of baseline serum creatinine, end-stage renal disease (ESRD; defined by serum creatinine ≥6 mg/dL, dialysis, or renal transplantation) or death. Treatment with AVAPRO resulted in a 20% risk reduction versus placebo (p=0.0234) (see Figure 3 and Table 1). Treatment with AVAPRO also reduced the occurrence of sustained doubling of serum creatinine as a separate endpoint (33%), but had no significant effect on ESRD alone and no effect on overall mortality (see Table 1).

The percentages of patients experiencing an event during the course of the study can be seen in Table 1 below:

Table 1: | IDNT: Components of Primary Composite Endpoint
 |  | Comparison With Placebo |  |  | Comparison With Amlodipine
 | AVAPRO N=579 (%) | Placebo N=569 (%) | Hazard Ratio | 95% CI | Amlodipine N=567 (%) | Hazard Ratio | 95% CI
Primary Composite Endpoint | 32.6 | 39.0 | 0.80 | 0.66-0.97 (p=0.0234) | 41.1 | 0.77 | 0.63-0.93
Breakdown of first occurring event contributing to primary endpoint
2x creatinine | 14.2 | 19.5 | --- | --- | 22.8 | --- | ---
ESRD | 7.4 | 8.3 | --- | --- | 8.8 | --- | ---
Death | 11.1 | 11.2 | --- | --- | 9.5 | --- | ----
Incidence of total events over entire period of follow-up
2x creatinine | 16.9 | 23.7 | 0.67 | 0.52-0.87 | 25.4 | 0.63 | 0.49-0.81
ESRD | 14.2 | 17.8 | 0.77 | 0.57-1.03 | 18.3 | 0.77 | 0.57-1.03
Death | 15.0 | 16.3 | 0.92 | 0.69-1.23 | 14.6 | 1.04 | 0.77-1.40

The secondary endpoint of the study was a composite of cardiovascular mortality and morbidity (myocardial infarction, hospitalization for heart failure, stroke with permanent neurological deficit, amputation). There were no statistically significant differences among treatment groups in these endpoints. Compared with placebo, AVAPRO significantly reduced proteinuria by about 27%, an effect that was evident within 3 months of starting therapy. AVAPRO significantly reduced the rate of loss of renal function (glomerular filtration rate), as measured by the reciprocal of the serum creatinine concentration, by 18.2%.

Table 2 presents results for demographic subgroups. Subgroup analyses are difficult to interpret and it is not known whether these observations represent true differences or chance effects. For the primary endpoint, AVAPRO’s favorable effects were seen in patients also taking other antihypertensive medications (angiotensin II receptor antagonists, angiotensin-converting-enzyme inhibitors and calcium channel blockers were not allowed), oral hypoglycemic agents, and lipid-lowering agents.

Table 2: | IDNT: Primary Efficacy Outcome Within Subgroups
 |  | Comparison With Placebo
Baseline Factors | AVAPRO N=579 (%) | Placebo N=569 (%) | Hazard Ratio | 95% Cl
Gender
Male | 27.5 | 36.7 | 0.68 | 0.53-0.88
Female | 42.3 | 44.6 | 0.98 | 0.72-1.34
Race
White | 29.5 | 37.3 | 0.75 | 0.60-0.95
Non-White | 42.6 | 43.5 | 0.95 | 0.67-1.34
Age (years)
<65 | 31.8 | 39.9 | 0.77 | 0.62-0.97
≥65 | 35.1 | 36.8 | 0.88 | 0.61-1.29

INDICATIONS AND USAGE

Hypertension

AVAPRO (irbesartan) is indicated for the treatment of hypertension. It may be used alone or in combination with other antihypertensive agents.

Nephropathy in Type 2 Diabetic Patients

AVAPRO is indicated for the treatment of diabetic nephropathy with an elevated serum creatinine and proteinuria (>300 mg/day) in patients with type 2 diabetes and hypertension. In this population, AVAPRO reduces the rate of progression of nephropathy as measured by the occurrence of doubling of serum creatinine or end-stage renal disease (need for dialysis or renal transplantation) (see CLINICAL PHARMACOLOGY: Clinical Studies).

CONTRAINDICATIONS

AVAPRO is contraindicated in patients who are hypersensitive to any component of this product.

WARNINGS

Fetal/Neonatal Morbidity and Mortality

Drugs that act directly on the renin-angiotensin system can cause fetal and neonatal morbidity and death when administered to pregnant women. Several dozen cases have been reported in the world literature in patients who were taking angiotensin-converting-enzyme inhibitors. When pregnancy is detected, AVAPRO should be discontinued as soon as possible.

The use of drugs that act directly on the renin-angiotensin system during the second and third trimesters of pregnancy has been associated with fetal and neonatal injury, including hypotension, neonatal skull hypoplasia, anuria, reversible or irreversible renal failure, and death. Oligohydramnios has also been reported, presumably resulting from decreased fetal renal function; oligohydramnios in this setting has been associated with fetal limb contractures, craniofacial deformation, and hypoplastic lung development. Prematurity, intrauterine growth retardation, and patent ductus arteriosus have also been reported, although it is not clear whether these occurrences were due to exposure to the drug.

These adverse effects do not appear to have resulted from intrauterine drug exposure that has been limited to the first trimester.

Mothers whose embryos and fetuses are exposed to an angiotensin II receptor antagonist only during the first trimester should be so informed. Nonetheless, when patients become pregnant, physicians should have the patient discontinue the use of AVAPRO as soon as possible.

Rarely (probably less often than once in every thousand pregnancies), no alternative to a drug acting on the renin-angiotensin system will be found. In these rare cases, the mothers should be apprised of the potential hazards to their fetuses, and serial ultrasound examinations should be performed to assess the intraamniotic environment.

If oligohydramnios is observed, AVAPRO should be discontinued unless it is considered life-saving for the mother. Contraction stress testing (CST), a non-stress test (NST), or biophysical profiling (BPP) may be appropriate depending upon the week of pregnancy. Patients and physicians should be aware, however, that oligohydramnios may not appear until after the fetus has sustained irreversible injury.

Infants with histories of in utero exposure to an angiotensin II receptor antagonist should be closely observed for hypotension, oliguria, and hyperkalemia. If oliguria occurs, attention should be directed toward support of blood pressure and renal perfusion. Exchange transfusion or dialysis may be required as a means of reversing hypotension and/or substituting for disordered renal function.

When pregnant rats were treated with irbesartan from day 0 to day 20 of gestation (oral doses of 50 mg/kg/day, 180 mg/kg/day, and 650 mg/kg/day), increased incidences of renal pelvic cavitation, hydroureter and/or absence of renal papilla were observed in fetuses at doses ≥50 mg/kg/day (approximately equivalent to the maximum recommended human dose [MRHD], 300 mg/day, on a body surface area basis). Subcutaneous edema was observed in fetuses at doses ≥180 mg/kg/day (about 4 times the MRHD on a body surface area basis). As these anomalies were not observed in rats in which irbesartan exposure (oral doses of 50, 150, and 450 mg/kg/day) was limited to gestation days 6 to 15, they appear to reflect late gestational effects of the drug. In pregnant rabbits, oral doses of 30 mg irbesartan/kg/day were associated with maternal mortality and abortion. Surviving females receiving this dose (about 1.5 times the MRHD on a body surface area basis) had a slight increase in early resorptions and a corresponding decrease in live fetuses. Irbesartan was found to cross the placental barrier in rats and rabbits.

Radioactivity was present in the rat and rabbit fetus during late gestation and in rat milk following oral doses of radiolabeled irbesartan.

Hypotension in Volume- or Salt-Depleted Patients

Excessive reduction of blood pressure was rarely seen (<0.1%) in patients with uncomplicated hypertension. Initiation of antihypertensive therapy may cause symptomatic hypotension in patients with intravascular volume- or sodium-depletion, eg, in patients treated vigorously with diuretics or in patients on dialysis. Such volume depletion should be corrected prior to administration of AVAPRO, or a low starting dose should be used (see DOSAGE AND ADMINISTRATION).

If hypotension occurs, the patient should be placed in the supine position and, if necessary, given an intravenous infusion of normal saline. A transient hypotensive response is not a contraindication to further treatment, which usually can be continued without difficulty once the blood pressure has stabilized.

PRECAUTIONS

Impaired Renal Function

As a consequence of inhibiting the renin-angiotensin-aldosterone system, changes in renal function may be anticipated in susceptible individuals. In patients whose renal function may depend on the activity of the renin-angiotensin-aldosterone system (eg, patients with severe congestive heart failure), treatment with angiotensin-converting-enzyme inhibitors has been associated with oliguria and/or progressive azotemia and (rarely) with acute renal failure and/or death. AVAPRO would be expected to behave similarly.

In studies of ACE inhibitors in patients with unilateral or bilateral renal artery stenosis, increases in serum creatinine or BUN have been reported. There has been no known use of AVAPRO in patients with unilateral or bilateral renal artery stenosis, but a similar effect should be anticipated.

Information for Patients

Pregnancy

Female patients of childbearing age should be told about the consequences of second- and third-trimester exposure to drugs that act on the renin-angiotensin system, and they should also be told that these consequences do not appear to have resulted from intrauterine drug exposure that has been limited to the first trimester. These patients should be asked to report pregnancies to their physicians as soon as possible.

Drug Interactions

No significant drug-drug pharmacokinetic (or pharmacodynamic) interactions have been found in interaction studies with hydrochlorothiazide, digoxin, warfarin, and nifedipine.

In vitro studies show significant inhibition of the formation of oxidized irbesartan metabolites with the known cytochrome CYP 2C9 substrates/inhibitors sulphenazole, tolbutamide and nifedipine. However, in clinical studies the consequences of concomitant irbesartan on the pharmacodynamics of warfarin were negligible. Based on in vitro data, no interaction would be expected with drugs whose metabolism is dependent upon cytochrome P450 isoenzymes 1A1, 1A2, 2A6, 2B6, 2D6, 2E1, or 3A4.

In separate studies of patients receiving maintenance doses of warfarin, hydrochlorothiazide, or digoxin, irbesartan administration for 7 days had no effect on the pharmacodynamics of warfarin (prothrombin time) or pharmacokinetics of digoxin. The pharmacokinetics of irbesartan were not affected by coadministration of nifedipine or hydrochlorothiazide.

Concomitant use of potassium-sparing diuretics, potassium supplements, or salt substitutes containing potassium may lead to increases in serum potassium.

Non-Steroidal Anti-Inflammatory Agents Including Selective Cyclooxygenase-2 Inhibitors (COX-2 Inhibitors)

In patients who are elderly, volume-depleted (including those on diuretic therapy), or with compromised renal function, coadministration of NSAIDs, including selective COX-2 inhibitors, with angiotensin II receptor antagonists, including irbesartan, may result in deterioration of renal function, including possible acute renal failure. These effects are usually reversible. Monitor renal function periodically in patients receiving irbesartan and NSAID therapy.

The antihypertensive effect of angiotensin II receptor antagonists, including irbesartan, may be attenuated by NSAIDs including selective COX-2 inhibitors.

Carcinogenesis, Mutagenesis, Impairment of Fertility

No evidence of carcinogenicity was observed when irbesartan was administered at doses of up to 500/1000 mg/kg/day (males/females, respectively) in rats and 1000 mg/kg/day in mice for up to 2 years. For male and female rats, 500 mg/kg/day provided an average systemic exposure to irbesartan (AUC0-24 hour, bound plus unbound) about 3 and 11 times, respectively, the average systemic exposure in humans receiving the maximum recommended dose (MRD) of 300 mg irbesartan/day, whereas 1000 mg/kg/day (administered to females only) provided an average systemic exposure about 21 times that reported for humans at the MRD. For male and female mice, 1000 mg/kg/day provided an exposure to irbesartan about 3 and 5 times, respectively, the human exposure at 300 mg/day.

Irbesartan was not mutagenic in a battery of in vitro tests (Ames microbial test, rat hepatocyte DNA repair test, V79 mammalian-cell forward gene-mutation assay). Irbesartan was negative in several tests for induction of chromosomal aberrations (in vitro-human lymphocyte assay; in vivo-mouse micronucleus study).

Irbesartan had no adverse effects on fertility or mating of male or female rats at oral doses ≤650 mg/kg/day, the highest dose providing a systemic exposure to irbesartan (AUC0-24 hour, bound plus unbound) about 5 times that found in humans receiving the maximum recommended dose of 300 mg/day.

Pregnancy

Pregnancy Categories C (first trimester) and D (second and third trimesters)

See WARNINGS: Fetal/Neonatal Morbidity and Mortality.

Nursing Mothers

It is not known whether irbesartan is excreted in human milk, but irbesartan or some metabolite of irbesartan is secreted at low concentration in the milk of lactating rats. Because of the potential for adverse effects on the nursing infant, a decision should be made whether to discontinue nursing or discontinue the drug, taking into account the importance of the drug to the mother.

Pediatric Use

Irbesartan, in a study at a dose of up to 4.5 mg/kg/day, once daily, did not appear to lower blood pressure effectively in pediatric patients ages 6 to 16 years.

AVAPRO has not been studied in pediatric patients less than 6 years old.

Geriatric Use

Of 4925 subjects receiving AVAPRO (irbesartan) in controlled clinical studies of hypertension, 911 (18.5%) were 65 years and over, while 150 (3.0%) were 75 years and over. No overall differences in effectiveness or safety were observed between these subjects and younger subjects, but greater sensitivity of some older individuals cannot be ruled out. (See CLINICAL PHARMACOLOGY: Pharmacokinetics, Special Populations, and Clinical Studies.)

ADVERSE REACTIONS

Hypertension

AVAPRO has been evaluated for safety in more than 4300 patients with hypertension and about 5000 subjects overall. This experience includes 1303 patients treated for over 6 months and 407 patients for 1 year or more. Treatment with AVAPRO was well-tolerated, with an incidence of adverse events similar to placebo. These events generally were mild and transient with no relationship to the dose of AVAPRO.

In placebo-controlled clinical trials, discontinuation of therapy due to a clinical adverse event was required in 3.3% of patients treated with AVAPRO, versus 4.5% of patients given placebo.

In placebo-controlled clinical trials, the following adverse event experiences reported in at least 1% of patients treated with AVAPRO (n=1965) and at a higher incidence versus placebo (n=641), excluding those too general to be informative and those not reasonably associated with the use of drug because they were associated with the condition being treated or are very common in the treated population, include: diarrhea (3% vs 2%), dyspepsia/heartburn (2% vs 1%), and fatigue (4% vs 3%).

The following adverse events occurred at an incidence of 1% or greater in patients treated with irbesartan, but were at least as frequent or more frequent in patients receiving placebo: abdominal pain, anxiety/nervousness, chest pain, dizziness, edema, headache, influenza, musculoskeletal pain, pharyngitis, nausea/vomiting, rash, rhinitis, sinus abnormality, tachycardia, and urinary tract infection.

Irbesartan use was not associated with an increased incidence of dry cough, as is typically associated with ACE inhibitor use. In placebo-controlled studies, the incidence of cough in irbesartan-treated patients was 2.8% versus 2.7% in patients receiving placebo.

The incidence of hypotension or orthostatic hypotension was low in irbesartan-treated patients (0.4%), unrelated to dosage, and similar to the incidence among placebo-treated patients (0.2%). Dizziness, syncope, and vertigo were reported with equal or less frequency in patients receiving irbesartan compared with placebo.

In addition, the following potentially important events occurred in less than 1% of the 1965 patients and at least 5 patients (0.3%) receiving irbesartan in clinical studies, and those less frequent, clinically significant events (listed by body system). It cannot be determined whether these events were causally related to irbesartan:

Body as a Whole: fever, chills, facial edema, upper extremity edema

Cardiovascular: flushing, hypertension, cardiac murmur, myocardial infarction, angina pectoris, arrhythmic/conduction disorder, cardio-respiratory arrest, heart failure, hypertensive crisis

Dermatologic: pruritus, dermatitis, ecchymosis, erythema face, urticaria

Endocrine/Metabolic/Electrolyte Imbalances: sexual dysfunction, libido change, gout

Gastrointestinal: constipation, oral lesion, gastroenteritis, flatulence, abdominal distention

Musculoskeletal/Connective Tissue: extremity swelling, muscle cramp, arthritis, muscle ache, musculoskeletal chest pain, joint stiffness, bursitis, muscle weakness

Nervous System: sleep disturbance, numbness, somnolence, emotional disturbance, depression, paresthesia, tremor, transient ischemic attack, cerebrovascular accident

Renal/Genitourinary: abnormal urination, prostate disorder

Respiratory: epistaxis, tracheobronchitis, congestion, pulmonary congestion, dyspnea, wheezing

Special Senses: vision disturbance, hearing abnormality, ear infection, ear pain, conjunctivitis, other eye disturbance, eyelid abnormality, ear abnormality

Nephropathy in Type 2 Diabetic Patients

In clinical studies in patients with hypertension and type 2 diabetic renal disease, the adverse drug experiences were similar to those seen in patients with hypertension with the exception of an increased incidence of orthostatic symptoms (dizziness, orthostatic dizziness, and orthostatic hypotension) observed in IDNT (proteinuria ≥900 mg/day, and serum creatinine ranging from 1.0-3.0 mg/dL). In this trial, orthostatic symptoms occurred more frequently in the AVAPRO group (dizziness 10.2%, orthostatic dizziness 5.4%, orthostatic hypotension 5.4%) than in the placebo group (dizziness 6.0%, orthostatic dizziness 2.7%, orthostatic hypotension 3.2%).

Post-Marketing Experience

The following adverse reactions have been identified during post-approval use of AVAPRO. Because these reactions are reported voluntarily from a population of uncertain size, it is not always possible to estimate reliably their frequency or to establish a causal relationship to drug exposure. Decisions to include these reactions in labeling are typically based on one or more of the following factors: (1) seriousness of the reaction, (2) frequency of reporting, or (3) strength of causal connection to AVAPRO.

The following have been reported: urticaria; angioedema (involving swelling of the face, lips, pharynx, and/or tongue); increased liver function tests; jaundice; hepatitis; hyperkalemia, and thrombocytopenia.

Impaired renal function, including cases of renal failure, has been reported.

Cases of increased CPK and rhabdomyolysis have been reported in patients receiving angiotensin II receptor blockers.

Laboratory Test Findings

Hypertension

In controlled clinical trials, clinically important differences in laboratory tests were rarely associated with administration of AVAPRO.

Creatinine, Blood Urea Nitrogen: Minor increases in blood urea nitrogen (BUN) or serum creatinine were observed in less than 0.7% of patients with essential hypertension treated with AVAPRO alone versus 0.9% on placebo. (See PRECAUTIONS: Impaired Renal Function.)

Hematologic: Mean decreases in hemoglobin of 0.2 g/dL were observed in 0.2% of patients receiving AVAPRO compared to 0.3% of placebo-treated patients. Neutropenia (<1000 cells/mm^3) occurred at similar frequencies among patients receiving AVAPRO (0.3%) and placebo-treated patients (0.5%).

Nephropathy in Type 2 Diabetic Patients

Hyperkalemia: In IDNT (proteinuria ≥900 mg/day, and serum creatinine ranging from 1.0-3.0 mg/dL), the percent of patients with hyperkalemia (>6 mEq/L) was 18.6% in the AVAPRO group versus 6.0% in the placebo group. Discontinuations due to hyperkalemia in the AVAPRO group were 2.1% versus 0.4% in the placebo group.

OVERDOSAGE

No data are available in regard to overdosage in humans. However, daily doses of 900 mg for 8 weeks were well-tolerated. The most likely manifestations of overdosage are expected to be hypotension and tachycardia; bradycardia might also occur from overdose. Irbesartan is not removed by hemodialysis.

To obtain up-to-date information about the treatment of overdosage, a good resource is a certified regional Poison Control Center. Telephone numbers of certified Poison Control Centers are listed in the Physicians’ Desk Reference (PDR). In managing overdose, consider the possibilities of multiple-drug interactions, drug-drug interactions, and unusual drug kinetics in the patient.

Laboratory determinations of serum levels of irbesartan are not widely available, and such determinations have, in any event, no known established role in the management of irbesartan overdose.

Acute oral toxicity studies with irbesartan in mice and rats indicated acute lethal doses were in excess of 2000 mg/kg, about 25- and 50-fold the MRHD (300 mg) on a mg/m^2 basis, respectively.

DOSAGE AND ADMINISTRATION

AVAPRO may be administered with other antihypertensive agents and with or without food.

Hypertension

The recommended initial dose of AVAPRO (irbesartan) is 150 mg once daily. Patients requiring further reduction in blood pressure should be titrated to 300 mg once daily.

A low dose of a diuretic may be added, if blood pressure is not controlled by AVAPRO alone. Hydrochlorothiazide has been shown to have an additive effect (see CLINICAL PHARMACOLOGY: Clinical Studies). Patients not adequately treated by the maximum dose of 300 mg once daily are unlikely to derive additional benefit from a higher dose or twice-daily dosing.

No dosage adjustment is necessary in elderly patients, or in patients with hepatic impairment or mild to severe renal impairment.

Nephropathy in Type 2 Diabetic Patients

The recommended target maintenance dose is 300 mg once daily. There are no data on the clinical effects of lower doses of AVAPRO on diabetic nephropathy (see CLINICAL PHARMACOLOGY: Clinical Studies).

Volume- and Salt-Depleted Patients

A lower initial dose of AVAPRO (75 mg) is recommended in patients with depletion of intravascular volume or salt (eg, patients treated vigorously with diuretics or on hemodialysis) (see WARNINGS: Hypotension in Volume- or Salt-Depleted Patients).

HOW SUPPLIED

AVAPRO® (irbesartan) is available as white to off-white biconvex oval tablets, debossed with a heart shape on one side and a portion of the NDC code on the other. Unit-of-use bottles contain 30, 90, or 500 tablets and blister packs contain 100 tablets, as follows:

 | 150 mg | 300 mg
Debossing | 2772 | 2773
Bottle of 30 | 54868-4199-0 | 54868-4414-0
Bottle of 60 | 54868-4199-2 | --
Bottle of 90 | 54868-4199-1 | 54868-4414-1

Storage

Store at 25°C (77°F); excursions permitted to 15°C-30°C (59°F-86°F) [see USP Controlled Room Temperature].

Distributed by:
Bristol-Myers Squibb Sanofi-Synthelabo Partnership
New York, NY 10016

1192327A6
1192328A6
Rev December 2011

Relabeling and Repackaging by:
Physicians Total Care, Inc.
Tulsa, Oklahoma 74146

PACKAGE LABEL

Avapro®
(irbesartan)
Tablets

150 mg

Rx only

PACKAGE LABEL

Avapro®
(irbesartan)
Tablets

300 mg

Rx only